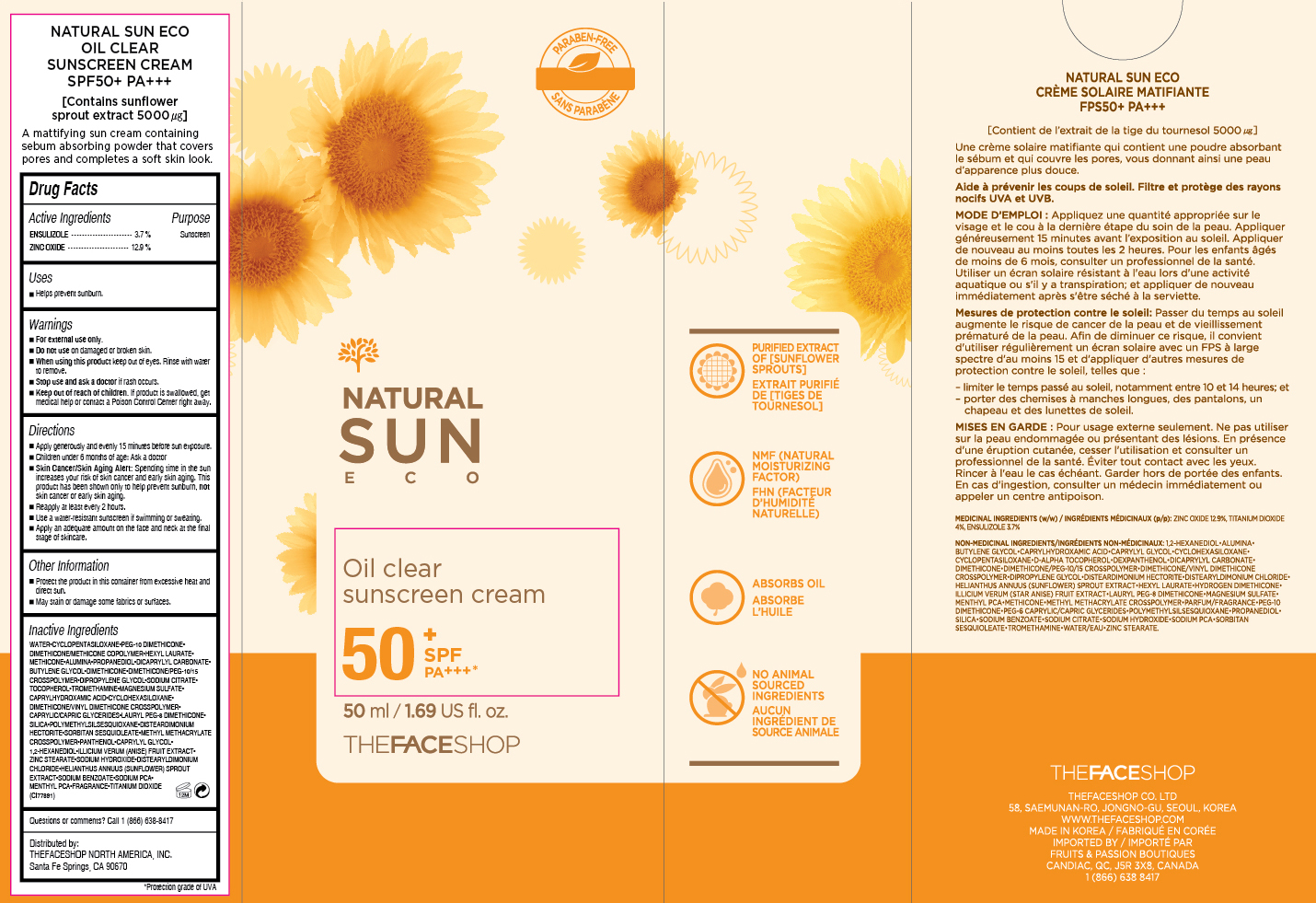 DRUG LABEL: NATURAL SUN ECO
NDC: 51523-193 | Form: CREAM
Manufacturer: THEFACESHOP CO., LTD.
Category: otc | Type: HUMAN OTC DRUG LABEL
Date: 20151002

ACTIVE INGREDIENTS: ENSULIZOLE 1.85 g/50 mL; ZINC OXIDE 6.45 g/50 mL
INACTIVE INGREDIENTS: WATER

NATURAL SUN ECO Oil Clear Sunscreen Cream 50+ PA+++ 31500193

Active Ingredients

Ensulizole 3.7 %
Zinc Oxide 12.9 %

Purpose

Sunscreen
Sunscreen

Uses

Helps prevent sunburn.

Warnings

For external use only.

Do not use on damaged or broken skin

When using this product keep out of eyes. Rinse with water to remove.

Stop use and ask a doctor if rash occurs.

Keep out of reach of children. If product is swallowed, get medical help or contact a Poison Control Center right away.

Directions

Apply generously and evenly 15 minutes before sun exposure.
Children under 6 months of age: Ask a doctor.
Skin Cancer/Skin Aging Alert: Spending time in the sun increases your risk of skin cancer and early skin aging. This product has been shown only to help prevent sunburn, not skin cancer or early skin aging.
Reapply at least every 2 hours.
Use a water-resistant sunscreen if swimming or sweating.

Apply an adequate amount on the face and neck at the final stage of skincare.

OTHER SAFETY INFORMATION

Protect the product in this container from excessive heat and direct sun.

May stain or damage some fabrics or surfaces.

Inactive Ingredients

WATER,CYCLOPENTASILOXANE, PEG-10 DIMETHICONE, DIMETHICONE/METHICONE COPOLYMER, HEXYL LAURATE, METHICONE, ALUMINA, PROPANEDIOL, DICAPRYLYL CARBONATE, BUTYLENE GLYCOL, DIMETHICONE, DIMETHICONE/PEG-10/15 CROSSPOLYMER, DIPROPYLENE GLYCOL, SODIUM CITRATE, TOCOPHEROL, TROMETHAMINE, MAGNESIUM SULFATE, CAPRYLHYDROXAMIC ACID, CYCLOHEXASILOXANE, DIMETHICONE/VINYL DIMETHICONE CROSSPOLYMER, CAPRYLIC/CAPRIC GLYCERIDES, LAURYL PEG-8 DIMETHICONE, SILICA, POLYMETHYLSILSESQUIOXANE, DISTEARDIMONIUM HECTORITE, SORBITAN SESQUIOLEATE, METHYL METHACRYLATE CROSSPOLYMER, PANTHENOL, CAPRYLYL GLYCOL, 1,2-HEXANEDIOL, ILLICIUM VERUM (ANISE) FRUIT EXTRACT, ZINC STEARATE, SODIUM HYDROXIDE, DISTEARYLDIMONIUM CHLORIDE, HELIANTHUS ANNUUS (SUNFLOWER) SPROUT EXTRACT, SODIUM BENZOATE, SODIUM PCA, MENTHYL PCA, FRAGRANCE , TITANIUM DIOXIDE (CI77891)

Questions or comments? Call 1-866-638-8417

Distributed by:

THEFACESHOP NORTH AMERICA, INC.

Santa Fe Springs, CA 90670

PACKAGE LABEL

NATURAL SUN ECO

Oil Clear Sunscreen Cream

SPF50+ PA+++

Contains sunflower sprout extract 5000 µg

A mattifying sun cream containing sebum absorbing powder that covers pores and completes a soft skin look.